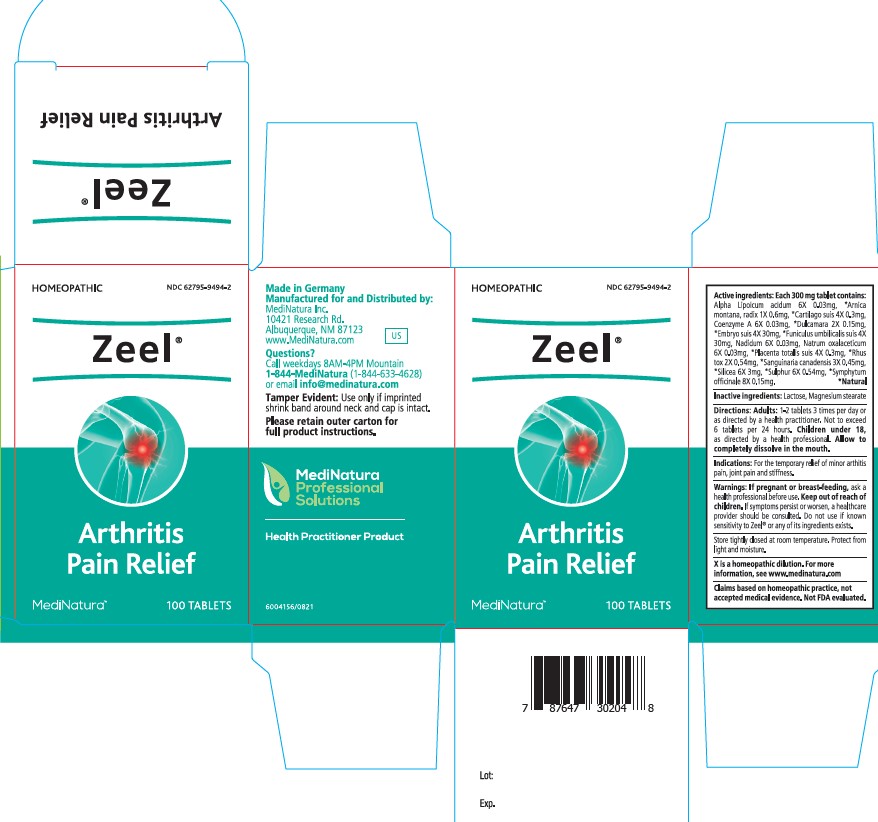 DRUG LABEL: Zeel
NDC: 62795-9494 | Form: TABLET
Manufacturer: MediNatura Inc
Category: homeopathic | Type: HUMAN OTC DRUG LABEL
Date: 20230928

ACTIVE INGREDIENTS: ALPHA LIPOIC ACID 6 [hp_X]/1 1; ARNICA MONTANA ROOT 1 [hp_X]/1 1; SUS SCROFA CARTILAGE 4 [hp_X]/1 1; COENZYME A 6 [hp_X]/1 1; SOLANUM DULCAMARA TOP 2 [hp_X]/1 1; SUS SCROFA EMBRYO 4 [hp_X]/1 1; SUS SCROFA UMBILICAL CORD 4 [hp_X]/1 1; NADIDE 6 [hp_X]/1 1; SODIUM DIETHYL OXALACETATE 6 [hp_X]/1 1; SUS SCROFA PLACENTA 4 [hp_X]/1 1; TOXICODENDRON PUBESCENS LEAF 2 [hp_X]/1 1; SANGUINARIA CANADENSIS ROOT 3 [hp_X]/1 1; SILICON DIOXIDE 6 [hp_X]/1 1; SULFUR 6 [hp_X]/1 1; COMFREY ROOT 8 [hp_X]/1 1
INACTIVE INGREDIENTS: LACTOSE, UNSPECIFIED FORM; MAGNESIUM STEARATE

Zeel

Indications:

For the temporary relief of minor arthitis
pain, joint pain and stiffness.

Warnings:

If pregnant or breast-feeding, ask a
health professional before use. Keep out of reach of
children. If symptoms persist or worsen, a healthcare
provider should be consulted. Do not use if known
sensitivity to Zeel® or any of its ingredients exists.

Directions:

Adults: 1-2 tablets 3 times per day or
as directed by a health practitioner. Not to exceed
6 tablets per 24 hours. Children under 18,
as directed by a health professional. Allow to
completely dissolve in the mouth.

Inactive ingredients:

Lactose, Magnesium stearate

KEEP OUT OF REACH OF CHILDREN

Purpose

Arthritis Pain
Relief

Active ingredients:

Each 300 mg tablet contains:
Alpha Lipoicum acidum 6X 0.03mg, *Arnica
montana, radix 1X 0.6mg, *Cartilago suis 4X 0.3mg,
Coenzyme A 6X 0.03mg, *Dulcamara 2X 0.15mg,
*Embryo suis 4X 30mg, *Funiculus umbilicalis suis 4X
30mg, Nadidum 6X 0.03mg, Natrum oxalaceticum
6X 0.03mg, *Placenta totalis suis 4X 0.3mg, *Rhus
tox 2X 0.54mg, *Sanguinaria canadensis 3X 0.45mg,
*Silicea 6X 3mg, *Sulphur 6X 0.54mg, *Symphytum
officinale 8X 0.15mg. *Natural